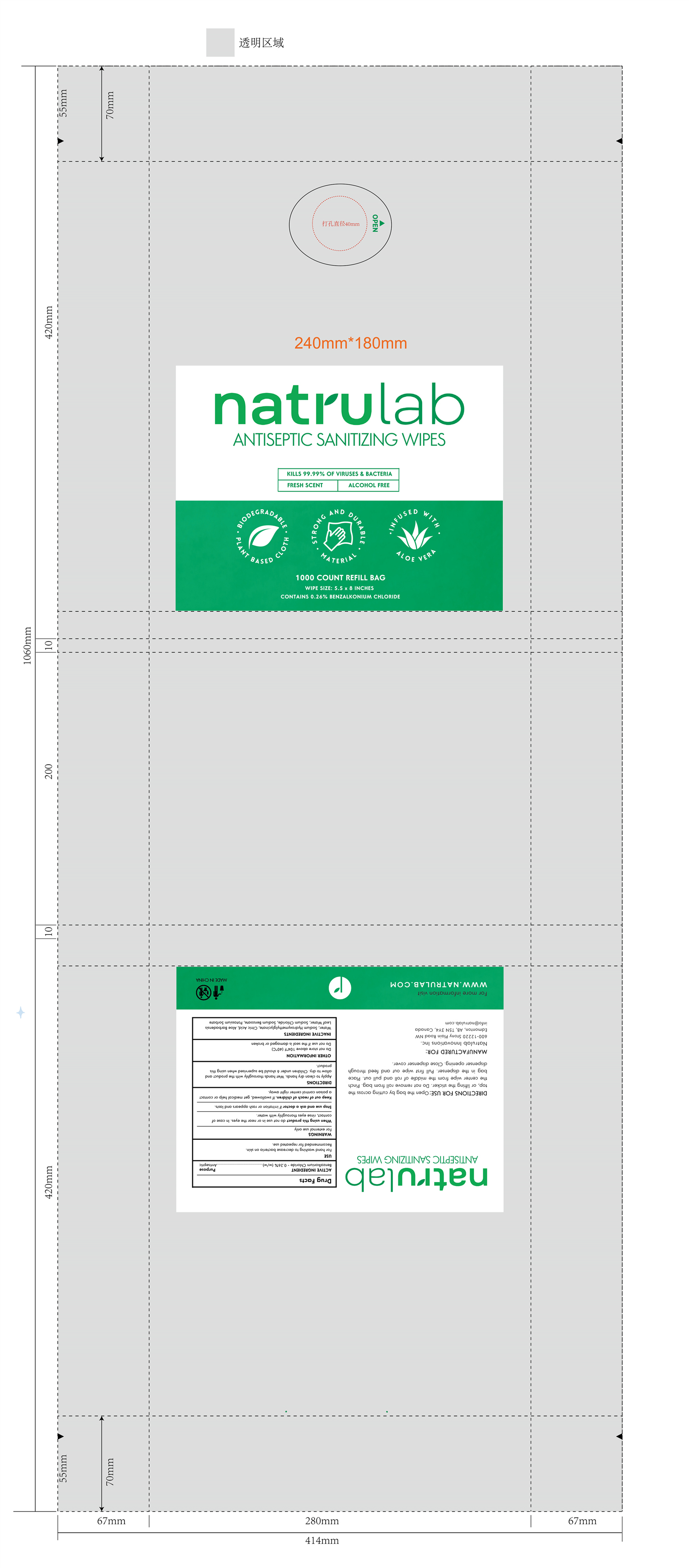 DRUG LABEL: NATRULAB ANTISEPTIC SANITIZING WIPES
NDC: 83086-001 | Form: CLOTH
Manufacturer: Natrulab Innovations Inc
Category: otc | Type: HUMAN OTC DRUG LABEL
Date: 20231105

ACTIVE INGREDIENTS: BENZALKONIUM CHLORIDE 0.26 g/100 g
INACTIVE INGREDIENTS: SODIUM HYDROXYMETHYLGLYCINATE; SODIUM CHLORIDE; WATER; POTASSIUM SORBATE; SODIUM BENZOATE; ALOE VERA LEAF; ANHYDROUS CITRIC ACID

83086-001 NATRULAB ANTISEPTIC SANITIZING WIPES

ACTIVE INGREDIENT

Benzalkonium Chloride - 0.26% (w/w)

Purpose

Antiseptic

USE

For hand washing to decrease bacteria on skin.

Recommended for repeated use.

WARNINGS

For external use only

When using this product do not use in or near the eyes. In case of contact, rinse eyes thoroughly with water.

Stop use and ask a doctor if irritation or rash appears and lasts.

Keep out of reach of children. If swallowed, get medical help or contact a poison control center right away.

When using this product do not use in or near the eyes. In case of contact, rinse eyes thoroughly with water.

Stop use and ask a doctor if irritation or rash appears and lasts.

Keep out of reach of children. If swallowed, get medical help or contact a poison control center right away.

DIRECTIONS

Apply to clean dry hands. Wet hands thoroughly with the product and allow to dry. Children under 6 should be supervised when using this product.

OTHER INFORMATION

Do not store above 104℉ (40℃)

Do not use if the seal is damaged or broken

INACTIVE INGREDIENTS

Water, Sodium Hydroxymethylglycinate, Citric Acid, Aloe Barbadensis Leaf Water, Sodium Chloride, Sodium Benzoate, Potassium Sorbate

PACKAGE LABEL

1000 COUNT REFILL BAG

NDC: 83086-001-01